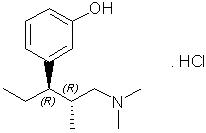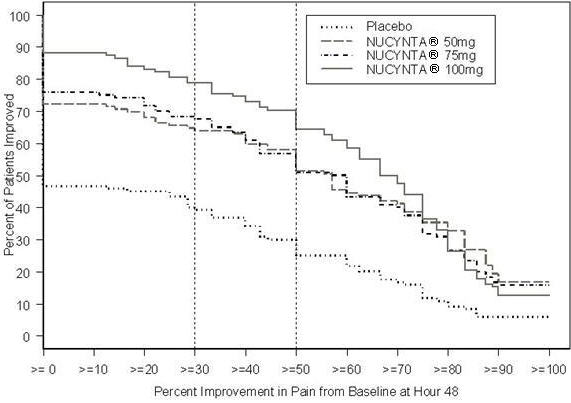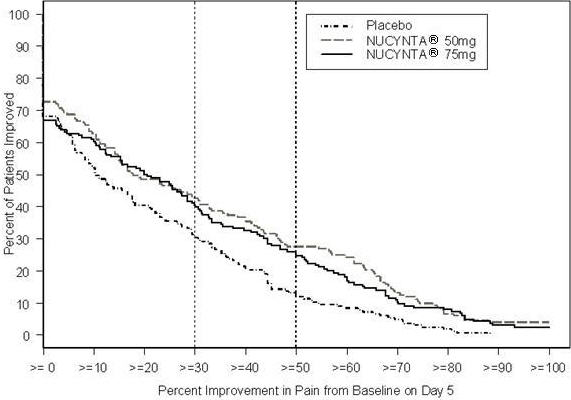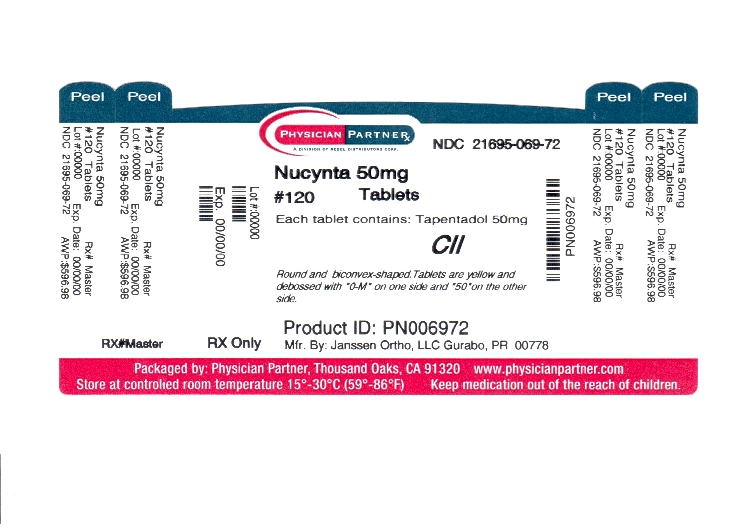 DRUG LABEL: NUCYNTA
NDC: 21695-069 | Form: TABLET, FILM COATED
Manufacturer: Rebel Distributors Corp
Category: prescription | Type: HUMAN PRESCRIPTION DRUG LABEL
Date: 20110729
DEA Schedule: CII

ACTIVE INGREDIENTS: tapentadol hydrochloride 50 mg/1 1
INACTIVE INGREDIENTS: CELLULOSE, MICROCRYSTALLINE; lactose monohydrate; croscarmellose sodium; povidone; magnesium stearate; polyvinyl alcohol; titanium dioxide; polyethylene glycol; talc; aluminum oxide

HIGHLIGHTS OF PRESCRIBING INFORMATION

These highlights do not include all the information needed to use NUCYNTA® safely and effectively. See full prescribing information for NUCYNTA®.
NUCYNTA® (tapentadol) immediate-release oral tablets C-II
Initial U.S. Approval: 2008

1 INDICATIONS AND USAGE

NUCYNTA® is an opioid analgesic indicated for the relief of moderate to severe acute pain in patients 18 years of age or older. (1)

2 DOSAGE AND ADMINISTRATION

- As with many centrally-acting analgesic medications, the dosing regimen of NUCYNTA® should be individualized according to the severity of pain being treated, the previous experience with similar drugs and the ability to monitor the patient. (2)
- Initiate NUCYNTA® with or without food at a dose of 50 mg, 75 mg, or 100 mg every 4 to 6 hours depending upon pain intensity. On the first day of dosing, the second dose may be administered as soon as one hour after the first dose, if adequate pain relief is not attained with the first dose. Subsequent dosing is 50 mg, 75 mg, or 100 mg every 4 to 6 hours and should be adjusted to maintain adequate analgesia with acceptable tolerability. Daily doses greater than 700 mg on the first day of therapy and 600 mg on subsequent days have not been studied and are, therefore, not recommended. (2)

3 DOSAGE FORMS AND STRENGTHS

Tablets: 50 mg, 75 mg, 100 mg (3)

4 CONTRAINDICATIONS

- Impaired pulmonary function (significant respiratory depression, acute or severe bronchial asthma or hypercapnia in unmonitored settings or the absence of resuscitative equipment) (4.1)
- Paralytic ileus (4.2)
- Concomitant use with monoamine oxidase inhibitors (MAOI) or use within 14 days (4.3)

5 WARNINGS AND PRECAUTIONS

- Respiratory depression: Increased risk in elderly, debilitated patients, those suffering from conditions accompanied by hypoxia, hypercapnia, or upper airway obstruction. (5.1)
- CNS effects: Additive CNS depressive effects when used in conjunction with alcohol, other opioids, or illicit drugs. (5.2)
- Elevation of intracranial pressure: May be markedly exaggerated in the presence of head injury, other intracranial lesions. (5.3)
- Abuse potential may occur. Monitor patients closely for signs of abuse and addiction. (5.4)
- Impaired mental/physical abilities: Caution must be used with potentially hazardous activities. (5.5)
- Seizures: Use with caution in patients with a history of seizures. (5.7)
- Serotonin Syndrome: Potentially life-threatening condition could result from concomitant serotonergic administration. (5.8)

6 ADVERSE REACTIONS

The most common adverse events were nausea, dizziness, vomiting and somnolence. (6)

To report SUSPECTED ADVERSE REACTIONS, contact PriCara, Division of Ortho-McNeil-Janssen Pharmaceuticals, Inc. at 1-800-526-7736 or FDA at 1-800-FDA-1088 or www.fda.gov/medwatch

7 DRUG INTERACTIONS

- Use NUCYNTA® with caution in patients currently using specified centrally-acting drugs or alcohol. (7.3)
- Do not use NUCYNTA® in patients currently using or within 14 days of using a monoamine oxidase inhibitor (MAOI). (7.4)

8 USE IN SPECIFIC POPULATIONS

- Labor and delivery: should not use during and immediately prior to labor and delivery. Monitor neonates, whose mothers have been taking NUCYNTA®, for respiratory depression. (8.2)
- Nursing mothers: should not breast-feed. (8.3)
- Pediatric use: safety and effectiveness not established in patients less than 18 years of age. (8.4)
- Renal or hepatic impairment: not recommended in patients with severe renal or hepatic impairment. Use with caution in patients with moderate hepatic impairment. (8.6, 8.7)
- Elderly: care should be taken when selecting an initial dose. (2.3)

FULL PRESCRIBING INFORMATION

NUCYNTA® (tapentadol) is indicated for the relief of moderate to severe acute pain in patients 18 years of age or older.

2 DOSAGE AND ADMINISTRATION

As with many centrally-acting analgesic medications, the dosing regimen should be individualized according to the severity of pain being treated, the previous experience with similar drugs and the ability to monitor the patient.

The dose is 50 mg, 75 mg, or 100 mg every 4 to 6 hours depending upon pain intensity.

On the first day of dosing, the second dose may be administered as soon as one hour after the first dose, if adequate pain relief is not attained with the first dose. Subsequent dosing is 50 mg, 75 mg, or 100 mg every 4 to 6 hours and should be adjusted to maintain adequate analgesia with acceptable tolerability.

Daily doses greater than 700 mg on the first day of therapy and 600 mg on subsequent days have not been studied and are not recommended.

NUCYNTA® may be given with or without food [see Clinical Pharmacology (12.3)].

2.1 Renal Impairment

No dosage adjustment is recommended in patients with mild or moderate renal impairment [see Clinical Pharmacology (12.3)].

NUCYNTA® has not been studied in patients with severe renal impairment. The use in this population is not recommended.

2.2 Hepatic Impairment

No dosage adjustment is recommended in patients with mild hepatic impairment [see Clinical Pharmacology (12.3)].

NUCYNTA® should be used with caution in patients with moderate hepatic impairment. Treatment in these patients should be initiated at 50 mg with the interval between doses no less than every 8 hours (maximum of three doses in 24 hours). Further treatment should reflect maintenance of analgesia with acceptable tolerability, to be achieved by either shortening or lengthening the dosing interval [see Clinical Pharmacology (12.3)].

NUCYNTA® has not been studied in patients with severe hepatic impairment and use in this population is not recommended [see Warnings and Precautions (5.10)].

2.3 Elderly Patients

In general, recommended dosing for elderly patients with normal renal and hepatic function is the same as for younger adult patients with normal renal and hepatic function. Because elderly patients are more likely to have decreased renal and hepatic function, consideration should be given to starting elderly patients with the lower range of recommended doses.

3 DOSAGE FORMS AND STRENGTHS

NUCYNTA® Tablets are round, biconvex and film-coated and are available in the following strengths, colors, and debossings: 50 mg of tapentadol (yellow with "O-M" on one side and "50" on the other side), 75 mg of tapentadol (yellow-orange with "O-M" on one side and "75" on the other side), and 100 mg of tapentadol (orange with "O-M" on one side and "100" on the other side).

4 CONTRAINDICATIONS

4.1 Impaired Pulmonary Function

Like other drugs with mu-opioid agonist activity, NUCYNTA® is contraindicated in patients with significant respiratory depression in unmonitored settings or the absence of resuscitative equipment. NUCYNTA® is also contraindicated in patients with acute or severe bronchial asthma or hypercapnia in unmonitored settings or the absence of resuscitative equipment [see Warnings and Precautions (5.1)].

4.2 Paralytic Ileus

Like drugs with mu-opioid agonist activity, NUCYNTA® is contraindicated in any patient who has or is suspected of having paralytic ileus.

4.3 Monoamine Oxidase Inhibitors

NUCYNTA® is contraindicated in patients who are receiving monoamine oxidase (MAO) inhibitors or who have taken them within the last 14 days due to potential additive effects on norepinephrine levels which may result in adverse cardiovascular events [see Drug Interactions (7.4)].

5 WARNINGS AND PRECAUTIONS

5.1 Respiratory Depression

Respiratory depression is the primary risk of mu-opioid agonists. Respiratory depression occurs more frequently in elderly or debilitated patients and in those suffering from conditions accompanied by hypoxia, hypercapnia, or upper airway obstruction, in whom even moderate therapeutic doses may significantly decrease pulmonary ventilation.

NUCYNTA® should be administered with caution to patients with conditions accompanied by hypoxia, hypercapnia or decreased respiratory reserve such as: asthma, chronic obstructive pulmonary disease or cor pulmonale, severe obesity, sleep apnea syndrome, myxedema, kyphoscoliosis, central nervous system (CNS) depression, or coma. In such patients, even usual therapeutic doses of NUCYNTA® may increase airway resistance and decrease respiratory drive to the point of apnea. Alternative non-mu-opioid agonist analgesics should be considered and NUCYNTA® should be employed only under careful medical supervision at the lowest effective dose in such patients. If respiratory depression occurs, it should be treated as any mu-opioid agonist-induced respiratory depression [see Overdosage (10.2)].

5.2 CNS Depression

Patients receiving other mu-opioid agonist analgesics, general anesthetics, phenothiazines, other tranquilizers, sedatives, hypnotics, or other CNS depressants (including alcohol) concomitantly with NUCYNTA® may exhibit additive CNS depression. Interactive effects resulting in respiratory depression, hypotension, profound sedation, coma or death may result if these drugs are taken in combination with NUCYNTA®. When such combined therapy is contemplated, a dose reduction of one or both agents should be considered.

5.3 Head Injury and Increased Intracranial Pressure

Opioid analgesics can raise cerebrospinal fluid pressure as a result of respiratory depression with carbon dioxide retention. Therefore, NUCYNTA® should not be used in patients who may be susceptible to the effects of raised cerebrospinal fluid pressure such as those with evidence of head injury and increased intracranial pressure. Opioid analgesics may obscure the clinical course of patients with head injury due to effects on pupillary response and consciousness. NUCYNTA® should be used with caution in patients with head injury, intracranial lesions, or other sources of preexisting increased intracranial pressure.

5.4 Misuse and Abuse

Tapentadol is a mu-opioid agonist and is a Schedule II controlled substance. Such drugs are sought by drug abusers and people with addiction disorders. Diversion of Schedule II products is an act subject to criminal penalty.

NUCYNTA® can be abused in a manner similar to other opioid agonists, legal or illicit. This should be considered when prescribing or dispensing NUCYNTA® in situations where the physician or pharmacist is concerned about an increased risk of misuse and abuse. Concerns about abuse and addiction should not prevent the proper management of pain. However, all patients treated with mu-opioid agonists require careful monitoring for signs of abuse and addiction, since use of mu-opioid agonist analgesic products carry the risk of addiction even under appropriate medical use [see Drug Abuse and Dependence (9.2)].

NUCYNTA® may be abused by crushing, chewing, snorting or injecting the product. These practices pose a significant risk to the abuser that could result in overdose and death [see Drug Abuse and Dependence (9)].

5.5 Driving and Operating Machinery

Patients should be cautioned that NUCYNTA® may impair the mental and/or physical abilities required for the performance of potentially hazardous tasks such as driving a car or operating machinery. This is to be expected especially at the beginning of treatment, at any change of dosage as well as in combination with alcohol or tranquilizers [see Drug Interactions (7.3)].

5.6 Interactions with Alcohol and Drugs of Abuse

Due to its mu-opioid agonist activity, NUCYNTA® may be expected to have additive effects when used in conjunction with alcohol, opioids, or illicit drugs that cause central nervous system depression, respiratory depression, hypotension, and profound sedation, coma or death [see Drug Interactions (7.3)].

5.7 Seizures

NUCYNTA® has not been systematically evaluated in patients with a seizure disorder, and such patients were excluded from clinical studies. NUCYNTA® should be prescribed with care in patients with a history of a seizure disorder or any condition that would put the patient at risk of seizures.

5.8 Serotonin Syndrome Risk

The development of a potentially life-threatening serotonin syndrome may occur with use of Serotonin and Norepinephrine Reuptake Inhibitor (SNRI) products, including NUCYNTA®, particularly with concomitant use of serotonergic drugs such as Selective Serotonin Reuptake Inhibitors (SSRIs), SNRIs, tricyclic antidepressants (TCAs), MAOIs and triptans, and with drugs that impair metabolism of serotonin (including MAOIs). This may occur within the recommended dose. Serotonin syndrome may include mental-status changes (e.g., agitation, hallucinations, coma), autonomic instability (e.g., tachycardia, labile blood pressure, hyperthermia), neuromuscular aberrations (e.g., hyperreflexia, incoordination) and/or gastrointestinal symptoms (e.g., nausea, vomiting, diarrhea).

5.9 Withdrawal

Withdrawal symptoms may occur if NUCYNTA® is discontinued abruptly. These symptoms may include: anxiety, sweating, insomnia, rigors, pain, nausea, tremors, diarrhea, upper respiratory symptoms, piloerection, and rarely, hallucinations. Withdrawal symptoms may be reduced by tapering NUCYNTA® [see Drug Abuse and Dependence (9.3)].

5.10 Hepatic Impairment

A study of NUCYNTA® in subjects with hepatic impairment showed higher serum concentrations than in those with normal hepatic function. NUCYNTA® should be used with caution in patients with moderate hepatic impairment [see Dosage and Administration (2.2) and Clinical Pharmacology (12.3)].

NUCYNTA® has not been studied in patients with severe hepatic impairment and, therefore, use in this population is not recommended.

5.11 Use in Pancreatic/Biliary Tract Disease

Like other drugs with mu-opioid agonist activity, NUCYNTA® may cause spasm of the sphincter of Oddi and should be used with caution in patients with biliary tract disease, including acute pancreatitis.

6 ADVERSE REACTIONS

The following treatment-emergent adverse events are discussed in more detail in other sections of the labeling:

- Respiratory Depression [see Contraindications (4.1) and Warnings and Precautions (5.1)]
- CNS Depression [see Warnings and Precautions (5.2)]

Because clinical studies are conducted under widely varying conditions, adverse event rates observed in the clinical studies of a drug cannot be directly compared to rates in the clinical studies of another drug and may not reflect the rates observed in clinical practice. A treatment-emergent adverse event refers to any untoward medical event associated with the use of the drug in humans, whether or not considered drug-related.

Based on data from nine Phase 2/3 studies that administered multiple doses (seven placebo- and/or active-controlled, one noncontrolled and one Phase 3 active-controlled safety study) the most common adverse events (reported by ≥10% in any NUCYNTA® dose group) were: nausea, dizziness, vomiting and somnolence.

The most common reasons for discontinuation due to adverse events in the studies described above (reported by ≥1% in any NUCYNTA® dose group) were dizziness (2.6% vs. 0.5%), nausea (2.3% vs. 0.6%), vomiting (1.4% vs. 0.2%), somnolence (1.3% vs. 0.2%) and headache (0.9% vs. 0.2%) for NUCYNTA®- and placebo-treated patients, respectively.

Seventy-six percent of NUCYNTA®-treated patients from the nine studies experienced adverse events.

NUCYNTA® was studied in multiple-dose, active- or placebo-controlled studies, or noncontrolled studies (n = 2178), in single-dose studies (n = 870), in open-label study extension (n = 483) and in Phase 1 studies (n = 597). Of these, 2034 patients were treated with doses of 50 mg to 100 mg of NUCYNTA® dosed every 4 to 6 hours.

The data described below reflect exposure to NUCYNTA® in 3161 patients, including 449 exposed for 45 days. NUCYNTA® was studied primarily in placebo- and active-controlled studies (n = 2266, and n = 2944, respectively). The population was 18 to 85 years old (mean age 46 years), 68% were female, 75% white and 67% were postoperative. Most patients received NUCYNTA® doses of 50 mg, 75 mg, or 100 mg every 4 to 6 hours.

6.1 Commonly-Observed Treatment-Emergent Adverse Events in Double-Blind Controlled Clinical Trials

Table 1 lists the adverse events reported in ≥1% or more of NUCYNTA®-treated patients with acute moderate to severe pain in the pooled safety data from nine Phase 2/3 studies that administered multiple doses (seven placebo- and/or active-controlled, one noncontrolled, and one Phase 3 active-controlled safety study).

Table 1 Treatment-Emergent Adverse Events [A treatment-emergent adverse event refers to any untoward medical event associated with the use of the drug in humans, whether or not considered drug-related.] Reported by ≥1% of NUCYNTA®-Treated Patients In Seven Phase 2/3 Placebo- and/or Oxycodone-Controlled, One Noncontrolled, and One Phase 3 Oxycodone-Controlled Safety, Multiple-Dose Clinical Studies
System/Organ Class |  | NUCYNTA® | Placebo
 | MedDRA Preferred Term | 21 mg – 120 mg | (n=619)
 |  | (n=2178) | %
 |  | %
Gastrointestinal disorders
 | Nausea | 30 | 13
 | Vomiting | 18 | 4
 | Constipation | 8 | 3
 | Dry mouth | 4 | <1
 | Dyspepsia | 2 | <1
General disorders and administration site conditions
 | Fatigue | 3 | <1
 | Feeling hot | 1 | <1
Infections and infestations
 | Nasopharyngitis | 1 | <1
 | Upper respiratory tract infection | 1 | <1
 | Urinary tract infection | 1 | <1
Metabolism and nutrition disorders
 | Decreased appetite | 2 | 0
Musculoskeletal and connective tissue disorders
 | Arthralgia | 1 | <1
Nervous system disorders
 | Dizziness | 24 | 8
 | Somnolence | 15 | 3
 | Tremor | 1 | <1
 | Lethargy | 1 | <1
Psychiatric disorders
 | Insomnia | 2 | <1
 | Confusional state | 1 | 0
 | Abnormal dreams | 1 | <1
 | Anxiety | 1 | <1
Skin and subcutaneous tissue disorders
 | Pruritus | 5 | 1
 | Hyperhidrosis | 3 | <1
 | Pruritus generalized | 3 | <1
 | Rash | 1 | <1
Vascular disorders
 | Hot flush | 1 | <1

6.2 Other Adverse Reactions Observed During the Premarketing Evaluation of NUCYNTA®

The following adverse drug reactions occurred in <1% of NUCYNTA®-treated patients in the pooled safety data from nine Phase 2/3 studies that administered multiple doses (seven were placebo- and/or active-controlled, one noncontrolled, and one Phase 3 active-controlled safety study):

Cardiac disorders: heart rate increased, heart rate decreased

Eye disorders: visual disturbance

Gastrointestinal disorders: abdominal discomfort, impaired gastric emptying

General disorders and administration site conditions: irritability, edema, drug withdrawal syndrome, feeling drunk

Immune system disorders: hypersensitivity

Investigations: gamma-glutamyltransferase increased, alanine aminotransferase increased, aspartate aminotransferase increased

Musculoskeletal and connective tissue disorders: involuntary muscle contractions, sensation of heaviness

Nervous system disorders: hypoesthesia, paresthesia, disturbance in attention, sedation, dysarthria, depressed level of consciousness, memory impairment, ataxia, presyncope, syncope, coordination abnormal, seizure

Psychiatric disorders: euphoric mood, disorientation, restlessness, agitation, nervousness, thinking abnormal

Renal and urinary disorders: urinary hesitation, pollakiuria

Respiratory, thoracic and mediastinal disorders: oxygen saturation decreased, cough, dyspnea, respiratory depression

Skin and subcutaneous tissue disorders: urticaria

Vascular disorders: blood pressure decreased

In the pooled safety data, the overall incidence of adverse reactions increased with increased dose of NUCYNTA®, as did the percentage of patients with adverse reactions of nausea, dizziness, vomiting, somnolence, and pruritus.

6.3 Post-marketing Experience

The following additional adverse reactions have been identified during post-approval use of NUCYNTA®. Because these reactions are reported voluntarily from a population of uncertain size, it is not always possible to estimate their frequency reliably.

Gastrointestinal disorders: diarrhea

Immune system disorders: angioedema

Nervous system disorders: headache

Psychiatric disorders: hallucination

7 DRUG INTERACTIONS

NUCYNTA® is mainly metabolized by glucuronidation. The following substances have been included in a set of interaction studies without any clinically significant finding: acetaminophen, acetylsalicylic acid, naproxen and probenecid [see Clinical Pharmacology (12.3)].

The pharmacokinetics of tapentadol were not affected when gastric pH or gastrointestinal motility were increased by omeprazole and metoclopramide, respectively [see Clinical Pharmacology (12.3)].

7.1 Drugs Metabolized by Cytochrome P450 Enzymes

In vitro investigations indicate that NUCYNTA® does not inhibit or induce P450 enzymes. Thus, clinically relevant interactions mediated by the cytochrome P450 system are unlikely to occur [see Clinical Pharmacology (12.3)].

7.2 Drugs That Inhibit or Induce Cytochrome P450 Enzymes

The major pathway of tapentadol metabolism is conjugation with glucuronic acid to produce glucuronides. To a lesser extent, tapentadol is additionally metabolized to N-desmethyl tapentadol (13%) by CYP2C9 and CYP2C19 to hydroxy tapentadol (2%) by CYP2D6, which are further metabolized by conjugation. Since only a minor amount of NUCYNTA® is metabolized via the oxidative pathway clinically relevant interactions mediated by the cytochrome P450 system are unlikely to occur [see Clinical Pharmacology (12.3)].

7.3 Centrally-Acting Drugs and Alcohol

Patients receiving other opioid agonist analgesics, general anesthetics, phenothiazines, antiemetics, other tranquilizers, sedatives, hypnotics, or other CNS depressants (including alcohol) concomitantly with NUCYNTA® may exhibit an additive CNS depression. Interactive effects resulting in respiratory depression, hypotension, profound sedation, or coma may result if these drugs are taken in combination with NUCYNTA®. When such combined therapy is contemplated, a dose reduction of one or both agents should be considered [see Warnings and Precautions (5.2) and (5.6)].

7.4 Monoamine Oxidase Inhibitors

NUCYNTA® is contraindicated in patients who are receiving monoamine oxidase (MAO) inhibitors or who have taken them within the last 14 days due to potential additive effects on norepinephrine levels which may result in adverse cardiovascular events [see Contraindications (4.3)].

8 USE IN SPECIFIC POPULATIONS

8.1 Pregnancy

Pregnancy Category C.

Tapentadol HCl was evaluated for teratogenic effects in pregnant rats and rabbits following intravenous and subcutaneous exposure during the period of embryofetal organogenesis. When tapentadol was administered twice daily by the subcutaneous route in rats at dose levels of 10, 20, or 40 mg/kg/day [producing up to 1 times the plasma exposure at the maximum recommended human dose (MRHD) of 700 mg/day based on an area under the time-curve (AUC) comparison], no teratogenic effects were observed. Evidence of embryofetal toxicity included transient delays in skeletal maturation (i.e. reduced ossification) at the 40 mg/kg/day dose which was associated with significant maternal toxicity. Administration of tapentadol HCl in rabbits at doses of 4, 10, or 24 mg/kg/day by subcutaneous injection [producing 0.2, 0.6, and 1.85 times the plasma exposure at the MRHD based on an AUC comparison] revealed embryofetal toxicity at doses ≥ 10 mg/kg/day. Findings included reduced fetal viability, skeletal delays and other variations. In addition, there were multiple malformations including gastroschisis/thoracogastroschisis, amelia/phocomelia, and cleft palate at doses ≥ 10 mg/kg/day and above, and ablepharia, encephalopathy, and spina bifida at the high dose of 24 mg/kg/day. Embryofetal toxicity, including malformations, may be secondary to the significant maternal toxicity observed in the study.

In a study of pre- and postnatal development in rats, oral administration of tapentadol at doses of 20, 50, 150, or 300 mg/kg/day to pregnant and lactating rats during the late gestation and early postnatal period [resulting in up to 1.7 times the plasma exposure at the MRHD on an AUC basis] did not influence physical or reflex development, the outcome of neurobehavioral tests or reproductive parameters. Treatment-related developmental delay was observed, including incomplete ossification, and significant reductions in pup body weights and body weight gains at doses associated with maternal toxicity (150 mg/kg/day and above). At maternal tapentadol doses ≥ 150 mg/kg/day, a dose-related increase in pup mortality was observed through postnatal Day 4.

There are no adequate and well controlled studies of NUCYNTA® in pregnant women. NUCYNTA® should be used during pregnancy only if the potential benefit justifies the potential risk to the fetus.

8.2 Labor and Delivery

The effect of tapentadol on labor and delivery in humans is unknown. NUCYNTA® is not recommended for use in women during and immediately prior to labor and delivery. Due to the mu-opioid receptor agonist activity of NUCYNTA®, neonates whose mothers have been taking NUCYNTA® should be monitored for respiratory depression. A specific opioid antagonist, such as naloxone, should be available for reversal of opioid induced respiratory depression in the neonate.

8.3 Nursing Mothers

There is insufficient/limited information on the excretion of tapentadol in human or animal breast milk. Physicochemical and available pharmacodynamic/toxicological data on tapentadol point to excretion in breast milk and risk to the suckling child cannot be excluded. NUCYNTA® should not be used during breast-feeding.

8.4 Pediatric Use

The safety and effectiveness of NUCYNTA® in pediatric patients less than 18 years of age have not been established. NUCYNTA® is not recommended in this population.

8.5 Geriatric Use

Of the total number of patients in Phase 2/3 double-blind, multiple-dose clinical studies of NUCYNTA®, 19% were 65 and over, while 5% were 75 and over. No overall differences in effectiveness were observed between these patients and younger patients. The rate of constipation was higher in subjects greater than or equal to 65 years than those less than 65 years (12% vs. 7%).

In general, recommended dosing for elderly patients with normal renal and hepatic function is the same as for younger adult patients with normal renal and hepatic function. Because elderly patients are more likely to have decreased renal and hepatic function, consideration should be given to starting elderly patients with the lower range of recommended doses [see Clinical Pharmacology (12.3)].

8.6 Renal Impairment

In patients with severe renal impairment, the safety and effectiveness of NUCYNTA® has not been established. NUCYNTA® is not recommended in this population [see Dosage and Administration (2.1)].

8.7 Hepatic Impairment

Administration of NUCYNTA® resulted in higher exposures and serum levels to tapentadol in subjects with impaired hepatic function compared to subjects with normal hepatic function [see Clinical Pharmacology (12.3)]. NUCYNTA® should be used with caution in patients with moderate hepatic impairment [see Dosage and Administration (2.2)].

NUCYNTA® has not been studied in patients with severe hepatic impairment, therefore, use of NUCYNTA® is not recommended in this population [see Warnings and Precautions (5.10)].

9 DRUG ABUSE AND DEPENDENCE

9.1 Controlled Substance

NUCYNTA® contains tapentadol, a mu-opioid agonist and is a Schedule II controlled substance. NUCYNTA® has an abuse potential similar to hydromorphone, can be abused and is subject to criminal diversion.

9.2 Abuse

Addiction is a primary, chronic, neurobiologic disease, with genetic, psychosocial, and environmental factors influencing its development and manifestations. It is characterized by behaviors that include one or more of the following: impaired control over drug use, compulsive use, continued use despite harm, and craving. Drug addiction is a treatable disease, utilizing a multidisciplinary approach, but relapse is common.

Concerns about abuse and addiction should not prevent the proper management of pain. However, all patients treated with opioids require careful monitoring for signs of abuse and addiction, because use of opioid analgesic products carries the risk of addiction even under appropriate medical use.

"Drug seeking" behavior is very common in addicts, and drug abusers. Drug-seeking tactics include emergency calls or visits near the end of office hours, refusal to undergo appropriate examination, testing or referral, repeated claims of loss of prescriptions, tampering with prescriptions and reluctance to provide prior medical records or contact information for other treating physician(s). "Doctor shopping" (visiting multiple prescribers) to obtain additional prescriptions is common among drug abusers and people suffering from untreated addiction. Preoccupation with achieving adequate pain relief can be appropriate behavior in a patient with poor pain control.

Abuse and addiction are separate and distinct from physical dependence and tolerance. Physicians should be aware that addiction may not be accompanied by concurrent tolerance and symptoms of physical dependence in all addicts. In addition, abuse of mu-opioid agonists can occur in the absence of true addiction and is characterized by misuse for non-medical purposes, often in combination with other psychoactive substances. Careful recordkeeping of prescribing information, including quantity, frequency, and renewal requests is strongly advised.

Abuse of NUCYNTA® poses a risk of overdose and death. This risk is increased with concurrent abuse of NUCYNTA® with alcohol and other substances. In addition, parenteral drug abuse is commonly associated with transmission of infectious diseases such as hepatitis and HIV.

Proper assessment of the patient, proper prescribing practices, periodic re-evaluation of therapy, and proper dispensing and storage are appropriate measures that help to limit abuse of drugs with mu-opioid agonist properties.

Infants born to mothers physically dependent on opioids will also be physically dependent and may exhibit respiratory difficulties and withdrawal symptoms [see Warnings and Precautions (5.1)]. Use of NUCYNTA® in this population has not been characterized. As NUCYNTA® has mu-opioid agonist activity, infants whose mothers have taken NUCYNTA®, should be carefully monitored.

9.3 Dependence

Tolerance is the need for increasing doses of opioids to maintain a defined effect such as analgesia (in the absence of disease progression or other external factors). Physical dependence is manifested by withdrawal symptoms after abrupt discontinuation of a drug or upon administration of an antagonist.

The opioid abstinence or withdrawal syndrome is characterized by some or all of the following: restlessness, lacrimation, rhinorrhea, yawning, perspiration, chills, myalgia, and mydriasis. Other symptoms also may develop, including irritability, anxiety, backache, joint pain, weakness, abdominal cramps, insomnia, nausea, anorexia, vomiting, diarrhea, increased blood pressure, respiratory rate, or heart rate.

Generally, tolerance and/or withdrawal are more likely to occur the longer a patient is on continuous opioid therapy. In a safety study where drug was administered up to 90 days, 82.7% of patients taking NUCYNTA® who stopped abruptly without initiating alternative therapy and were assessed 2 to 4 days after discontinuation, did not have objective signs of opioid withdrawal using the Clinical Opiate Withdrawal Scale. Moderate withdrawal symptoms were seen in 0.3% of patients with the rest (17%) experiencing mild symptoms. Withdrawal symptoms may be reduced by tapering NUCYNTA®.

10 OVERDOSAGE

10.1 Human Experience

Experience with NUCYNTA® overdose is very limited. Preclinical data suggest that symptoms similar to those of other centrally acting analgesics with mu-opioid agonist activity are to be expected upon intoxication with tapentadol. In principle, these symptoms may particularly appear in the clinical setting: miosis, vomiting, cardiovascular collapse, consciousness disorders up to coma, convulsions and respiratory depression up to respiratory arrest.

10.2 Management of Overdose

Management of overdose should be focused on treating symptoms of mu-opioid agonism. Primary attention should be given to re-establishment of a patent airway and institution of assisted or controlled ventilation when overdose of NUCYNTA® is suspected. Supportive measures (including oxygen and vasopressors) should be employed in the management of circulatory shock and pulmonary edema accompanying overdose as indicated. Cardiac arrest or arrhythmias may require cardiac massage or defibrillation.

Pure opioid antagonists, such as naloxone, are specific antidotes to respiratory depression resulting from opioid overdose. Respiratory depression following an overdose may outlast the duration of action of the opioid antagonist. Administration of an opioid antagonist is not a substitute for continuous monitoring of airway, breathing, and circulation following an opioid overdose. If the response to opioid antagonists is suboptimal or only brief in nature, an additional antagonist should be administered as directed by the manufacturer of the product.

Gastrointestinal decontamination may be considered in order to eliminate unabsorbed drug. Gastrointestinal decontamination with activated charcoal or by gastric lavage is only recommended within 2 hours after intake. Gastrointestinal decontamination at a later time point may be useful in case of intoxication with exceptionally large quantities. Before attempting gastrointestinal decontamination, care should be taken to secure the airway.

11 DESCRIPTION

NUCYNTA® (tapentadol) Tablets are immediate-release film-coated tablets for oral administration. The chemical name is 3-[(1R,2R)-3-(dimethylamino)-1-ethyl-2-methylpropyl]phenol monohydrochloride. The structural formula is:

The molecular weight of tapentadol HCl is 257.80, and the molecular formula is C14H23NO•HCl. The n-octanol:water partition coefficient log P value is 2.87. The pKa values are 9.34 and 10.45. In addition to the active ingredient tapentadol HCl, tablets also contain the following inactive ingredients: microcrystalline cellulose, lactose monohydrate, croscarmellose sodium, povidone, magnesium stearate, and Opadry® II, a proprietary film-coating mixture containing polyvinyl alcohol, titanium dioxide, polyethylene glycol, talc, and aluminum lake coloring.

12 CLINICAL PHARMACOLOGY

12.1 Mechanism of Action

Tapentadol is a centrally-acting synthetic analgesic. Although its exact mechanism is unknown, analgesic efficacy is thought to be due to mu-opioid agonist activity and the inhibition of norepinephrine reuptake.

12.2 Pharmacodynamics

Tapentadol is a centrally-acting synthetic analgesic. It is 18 times less potent than morphine in binding to the human mu-opioid receptor and is 2–3 times less potent in producing analgesia in animal models. Tapentadol has been shown to inhibit norepinephrine reuptake in the brains of rats resulting in increased norepinephrine concentrations. In preclinical models, the analgesic activity due to the mu-opioid receptor agonist activity of tapentadol can be antagonized by selective mu-opioid antagonists (e.g., naloxone), whereas the norepinephrine reuptake inhibition is sensitive to norepinephrine modulators. Tapentadol exerts its analgesic effects without a pharmacologically active metabolite.

Effects on the cardiovascular system: There was no effect of therapeutic and supratherapeutic doses of tapentadol on the QT interval. In a randomized, double-blind, placebo- and positive-controlled crossover study, healthy subjects were administered five consecutive doses of NUCYNTA® 100 mg every 6 hours, NUCYNTA® 150 mg every 6 hours, placebo and a single oral dose of moxifloxacin. Similarly, NUCYNTA® had no relevant effect on other ECG parameters (heart rate, PR interval, QRS duration, T-wave or U-wave morphology).

12.3 Pharmacokinetics

Absorption

Mean absolute bioavailability after single-dose administration (fasting) is approximately 32% due to extensive first-pass metabolism. Maximum serum concentrations of tapentadol are typically observed at around 1.25 hours after dosing.

Dose-proportional increases in the Cmax and AUC values of tapentadol have been observed over the 50 to 150 mg dose range.

A multiple (every 6 hour) dose study with doses ranging from 75 to 175 mg tapentadol showed a mean accumulation factor of 1.6 for the parent drug and 1.8 for the major metabolite tapentadol-O-glucuronide, which are primarily determined by the dosing interval and apparent half-life of tapentadol and its metabolite.

Food Effect

The AUC and Cmax increased by 25% and 16%, respectively, when NUCYNTA® was administered after a high-fat, high-calorie breakfast. NUCYNTA® may be given with or without food.

Distribution

Tapentadol is widely distributed throughout the body. Following intravenous administration, the volume of distribution (Vz) for tapentadol is 540 +/- 98 L. The plasma protein binding is low and amounts to approximately 20%.

Metabolism and Elimination

In humans, the metabolism of tapentadol is extensive. About 97% of the parent compound is metabolized. Tapentadol is mainly metabolized via Phase 2 pathways, and only a small amount is metabolized by Phase 1 oxidative pathways. The major pathway of tapentadol metabolism is conjugation with glucuronic acid to produce glucuronides. After oral administration approximately 70% (55% O-glucuronide and 15% sulfate of tapentadol) of the dose is excreted in urine in the conjugated form. A total of 3% of drug was excreted in urine as unchanged drug. Tapentadol is additionally metabolized to N-desmethyl tapentadol (13%) by CYP2C9 and CYP2C19 and to hydroxy tapentadol (2%) by CYP2D6, which are further metabolized by conjugation. Therefore, drug metabolism mediated by cytochrome P450 system is of less importance than phase 2 conjugation.

None of the metabolites contributes to the analgesic activity.

Tapentadol and its metabolites are excreted almost exclusively (99%) via the kidneys. The terminal half-life is on average 4 hours after oral administration. The total clearance is 1530 +/- 177 ml/min.

Special Populations

Elderly

The mean exposure (AUC) to tapentadol was similar in elderly subjects compared to young adults, with a 16% lower mean Cmax observed in the elderly subject group compared to young adult subjects.

Renal Impairment

AUC and Cmax of tapentadol were comparable in subjects with varying degrees of renal function (from normal to severely impaired). In contrast, increasing exposure (AUC) to tapentadol-O-glucuronide was observed with increasing degree of renal impairment. In subjects with mild, moderate, and severe renal impairment, the AUC of tapentadol-O-glucuronide are 1.5-, 2.5-, and 5.5-fold higher compared with normal renal function, respectively.

Hepatic Impairment

Administration of NUCYNTA® resulted in higher exposures and serum levels to tapentadol in subjects with impaired hepatic function compared to subjects with normal hepatic function. The ratio of tapentadol pharmacokinetic parameters for the mild and moderate hepatic impairment groups in comparison to the normal hepatic function group were 1.7 and 4.2, respectively, for AUC; 1.4 and 2.5, respectively, for Cmax; and 1.2 and 1.4, respectively, for t1/2. The rate of formation of tapentadol-O-glucuronide was lower in subjects with increased liver impairment.

Pharmacokinetic Drug Interactions

Tapentadol is mainly metabolized by Phase 2 glucuronidation, a high capacity/low affinity system, therefore, clinically relevant interactions caused by Phase 2 metabolism are unlikely to occur. Naproxen and probenecid increased the AUC of tapentadol by 17% and 57%, respectively. These changes are not considered clinically relevant and no change in dose is required.

No changes in the pharmacokinetic parameters of tapentadol were observed when acetaminophen and acetylsalicylic acid were given concomitantly.

In vitro studies did not reveal any potential of tapentadol to either inhibit or induce cytochrome P450 enzymes. Thus, clinically relevant interactions mediated by the cytochrome P450 system are unlikely to occur.

The pharmacokinetics of tapentadol were not affected when gastric pH or gastrointestinal motility were increased by omeprazole and metoclopramide, respectively.

Plasma protein binding of tapentadol is low (approximately 20%). Therefore, the likelihood of pharmacokinetic drug-drug interactions by displacement from the protein binding site is low.

13 NONCLINICAL TOXICOLOGY

13.1 Carcinogenesis, Mutagenesis, Impairment of Fertility

Carcinogenesis

Tapentadol was administered to rats (diet) and mice (oral gavage) for two years.

In mice, tapentadol HCl was administered by oral gavage at dosages of 50, 100 and 200 mg/kg/day for 2 years (up to 0.2 times the plasma exposure at the maximum recommended human dose [MRHD] on an area under the time-curve [AUC] basis). No increase in tumor incidence was observed at any dose level.

In rats, tapentadol HCl was administered in diet at dosages of 10, 50, 125 and 250 mg/kg/day for two years (up to 0.2 times in the male rats and 0.6 times in the female rats the MRHD on an AUC basis). No increase in tumor incidence was observed at any dose level.

Mutagenesis

Tapentadol did not induce gene mutations in bacteria, but was clastogenic with metabolic activation in a chromosomal aberration test in V79 cells. The test was repeated and was negative in the presence and absence of metabolic activation. The one positive result for tapentadol was not confirmed in vivo in rats, using the two endpoints of chromosomal aberration and unscheduled DNA synthesis, when tested up to the maximum tolerated dose.

Impairment of Fertility

Tapentadol HCl was administered intravenously to male or female rats at dosages of 3, 6, or 12 mg/kg/day (representing exposures of up to approximately 0.4 times the exposure at the MRHD on an AUC basis, based on extrapolation from toxicokinetic analyses in a separate 4-week intravenous study in rats). Tapentadol did not alter fertility at any dose level. Maternal toxicity and adverse effects on embryonic development, including decreased number of implantations, decreased numbers of live conceptuses, and increased pre- and post-implantation losses occurred at dosages ≥6 mg/kg/day.

13.2 Animal Toxicology and/or Pharmacology

In toxicological studies with tapentadol, the most common systemic effects of tapentadol were related to the mu-opioid receptor agonist and norepinephrine reuptake inhibition pharmacodynamic properties of the compound. Transient, dose-dependent and predominantly CNS-related findings were observed, including impaired respiratory function and convulsions, the latter occurring in the dog at plasma levels (Cmax) which are in the range associated with the maximum recommended human dose (MRHD).

14 CLINICAL STUDIES

The efficacy and safety of NUCYNTA® in the treatment of moderate to severe acute pain has been established in two randomized, double-blind, placebo- and active-controlled studies of moderate to severe pain from first metatarsal bunionectomy and end-stage degenerative joint disease.

14.1 Orthopedic Surgery – Bunionectomy

A randomized, double-blind, parallel-group, active- and placebo-controlled, multiple-dose study demonstrated the efficacy of 50 mg, 75 mg, and 100 mg NUCYNTA® given every 4 to 6 hours for 72 hours in patients aged 18 to 80 years experiencing moderate to severe pain following unilateral, first metatarsal bunionectomy surgery. Patients who qualified for the study with a baseline pain score of ≥4 on an 11-point rating scale ranging from 0 to 10 were randomized to 1 of 5 treatments. Patients were allowed to take a second dose of study medication as soon as 1 hour after the first dose on study Day 1, with subsequent dosing every 4 to 6 hours. If rescue analgesics were required, the patients were discontinued for lack of efficacy. Efficacy was evaluated by comparing the sum of pain intensity difference over the first 48 hours (SPID48) versus placebo. NUCYNTA® at each dose provided a greater reduction in pain compared to placebo based on SPID48 values.

For various degrees of improvement from baseline to the 48-hour endpoint, Figure 1 shows the fraction of patients achieving that level of improvement. The figures are cumulative, such that every patient that achieves a 50% reduction in pain from baseline is included in every level of improvement below 50%. Patients who did not complete the 48-hour observation period in the study were assigned 0% improvement.

BOXED WARNING

Figure 1: Percentage of Patients Achieving Various Levels of Pain Relief as Measured by Pain Severity at 48 Hours Compared to Baseline- Post Operative Bunionectomy

The proportions of patients who showed reduction in pain intensity at 48 hours of 30% or greater, or 50% or greater were significantly higher in patients treated with NUCYNTA® at each dose versus placebo.

14.2 End-Stage Degenerative Joint Disease

A randomized, double-blind, parallel-group, active- and placebo-controlled, multiple-dose study evaluated the efficacy and safety of 50 mg and 75 mg NUCYNTA® given every 4 to 6 hours during waking hours for 10 days in patients aged 18 to 80 years, experiencing moderate to severe pain from end stage degenerative joint disease of the hip or knee, defined as a 3-day mean pain score of ≥5 on an 11-point pain intensity scale, ranging from 0 to 10. Pain scores were assessed twice daily and assessed the pain the patient had experienced over the previous 12 hours. Patients were allowed to continue non-opioid analgesic therapy for which they had been on a stable regimen before screening throughout the study. Eighty-three percent (83%) of patients in the tapentadol treatment groups and the placebo group took such analgesia during the study. The 75 mg treatment group was dosed at 50 mg for the first day of the study, followed by 75 mg for the remaining nine days. Patients requiring rescue analgesics other than study medication were discontinued for lack of efficacy. Efficacy was evaluated by comparing the sum of pain intensity difference (SPID) versus placebo over the first five days of treatment. NUCYNTA® 50 mg and 75 mg provided improvement in pain compared with placebo based on the 5-Day SPID.

For various degrees of improvement from baseline to the Day 5 endpoint, Figure 2 shows the fraction of patients achieving that level of improvement. The figures are cumulative, such that every patient that achieves a 50% reduction in pain from baseline is included in every level of improvement below 50%. Patients who did not complete the 5-day observation period in the study were assigned 0% improvement.

BOXED WARNING

Figure 2: Percentage of Patients Achieving Various Levels of Pain Relief as Measured by Average Pain Severity for the Previous 12 hours, Measured on Study Day 5 Compared to Baseline -- End Stage Degenerative Joint Disease

The proportions of patients who showed reduction in pain intensity at 5 days of 30% or greater, or 50% or greater were significantly higher in patients treated with NUCYNTA® at each dose versus placebo.

16 HOW SUPPLIED/STORAGE AND HANDLING

NUCYNTA® Tablets are available in the following strengths and packages. All tablets are round and biconvex-shaped.

50 mg tablets are yellow and debossed with "O-M" on one side and "50" on the other side, and are available in bottles of 120 (NDC 21695-069-72).

STORAGE AND HANDLING

Store up to 25ºC (77ºF); excursions permitted to 15º – 30ºC (59º – 86ºF) [see USP Controlled Room Temperature]. Protect from moisture.

Keep out of reach of children.

17 PATIENT COUNSELING INFORMATION

Physicians are advised to discuss the following issues with patients for whom they prescribe NUCYNTA®:

17.1 Instructions for Use

Patients should be advised NUCYNTA® should be taken only as directed and to report episodes of breakthrough pain and adverse experiences occurring during therapy to their physician. Individualization of dosage is essential to make optimal use of this medication. Patients should be advised not to adjust the dose of NUCYNTA® without consulting their physician [see Dosage and Administration (2)]. Patients should be advised that it may be appropriate to taper dosing when discontinuing treatment with NUCYNTA® as withdrawal symptoms may occur [see Drug Abuse and Dependence (9.3)]. The physician can provide a dose schedule to accomplish a gradual discontinuation of the medication.

17.2 Misuse and Abuse

Patients should be advised that NUCYNTA® is a potential drug of abuse. Patients should protect NUCYNTA® from theft, and NUCYNTA® should never be given to anyone other than the individual for whom NUCYNTA® was prescribed [see Warnings and Precautions (5.4)].

17.3 Interference with Cognitive and Motor Performance

As NUCYNTA® has the potential to impair judgment, thinking, or motor skills, patients should be cautioned about operating hazardous machinery, including automobiles [see Warnings and Precautions (5.5)].

17.4 Pregnancy

Patients should be advised to notify their physician if they become pregnant or intend to become pregnant during treatment with NUCYNTA® [see Use in Specific Populations (8.1)].

17.5 Nursing

Patients should be advised not to breast-feed an infant during treatment with NUCYNTA® [see Use in Specific Populations (8.3)].

17.6 Monoamine Oxidase Inhibitors

Patients should be informed not to take NUCYNTA® while using any drugs that inhibit monoamine oxidase. Patients should not start any new medications while taking NUCYNTA® until they are assured by their healthcare provider that the new medication is not a monoamine oxidase inhibitor.

17.7 Seizures

Patients should be informed that NUCYNTA® could cause seizures if they are at risk for seizures or have epilepsy. Such patients should be advised to use NUCYNTA® with care [see Warnings and Precautions (5.7)]. Patients should be advised to stop taking NUCYNTA® if they have a seizure while taking NUCYNTA® and call their healthcare provider right away.

17.8 Serotonin Syndrome

Patients should be informed that NUCYNTA® could cause rare but potentially life-threatening conditions resulting from concomitant administration of serotonergic drugs (including Serotonin Reuptake Inhibitors, Serotonin and Norepinephrine Reuptake Inhibitors and tricyclic antidepressants) [see Warnings and Precautions (5.8)].

Patients should be advised to inform their physicians if they are taking, or plan to take, any prescription or over-the-counter drugs as there is a potential for interactions [see Drug Interactions (7)].

17.9 Alcohol

Patients should be advised to avoid alcohol while taking NUCYNTA® [see Drug Interactions (7.3)].

17.10 Medication Guide

See Medication Guide.

Revised: March 2011

Manufactured by:
Janssen Ortho, LLC
Gurabo, PR 00778

Manufactured for:
PriCara®, Division of Ortho-McNeil-Janssen Pharmaceuticals, Inc.
Raritan, NJ 08869

© Ortho-McNeil-Janssen Pharmaceuticals, Inc. 2009

Repackaged by:

Rebel Distributors Corp

Thousand Oaks, CA 91320

MEDICATION GUIDE

NUCYNTA® (new-SINN-tah)

(tapentadol)

immediate-release oral tablets C-II

BOXED WARNING

- NUCYNTA® is a federally controlled substance (C-II) because it can be abused. Keep NUCYNTA® in a safe place to prevent theft. Selling or giving away NUCYNTA® may harm others, and is against the law.
- Tell your doctor if you (or a family member) have ever abused or been dependent on alcohol, prescription medicines, or street drugs.

Read the Medication Guide that comes with NUCYNTA® before you start taking it and each time you get a new prescription. There may be new information. This Medication Guide does not take the place of talking to your doctor about your medical condition or your treatment. Talk to your doctor if you have any questions.

What is the most important information I should know about NUCYNTA®?

NUCYNTA® is a tablet that contains tapentadol, a strong medicine that is a pain medicine.

Use NUCYNTA® exactly how your doctor tells you to. Do not use NUCYNTA® if it has not been prescribed for you.

You should not take NUCYNTA® if your pain is mild and can be controlled with other pain medicines such as non-steroidal anti-inflammatory medicines (NSAIDS) or acetaminophen.

What is NUCYNTA®?

- NUCYNTA® is a prescription medicine that is used in adults 18 years of age or older to treat moderate to severe pain that is expected to last a short time.
  NUCYNTA® is for short-term use only because the risks for withdrawal symptoms, abuse and addiction are higher when NUCYNTA® is used longer.

Who should not take NUCYNTA®?

Do not take NUCYNTA® if you:

- have severe lung problems
- have a gastrointestinal problem called paralytic ileus in which the intestines are not working normally.
- take a monoamine oxidase inhibitor (MAOI) medicine or have taken an MAOI within the last 14 days. Ask your doctor or pharmacist if any of your medicines is an MAOI.

What should I tell my doctor before taking NUCYNTA®?

NUCYNTA® may not be right for you. Tell your doctor about all your medical conditions, including if you have:

- trouble breathing or lung problems
- or had a head injury
- liver or kidney problems
- convulsions or seizures
- dependency problems with alcohol
- pancreas or gall bladder problems
- past or present substance abuse or drug addiction. There is a risk of abuse or addiction with narcotic pain medicines. If you have abused drugs in the past, you may have a higher chance of developing abuse or addiction again while using NUCYNTA®.
- are pregnant or plan to become pregnant
- are breast-feeding. You should not breast-feed while taking NUCYNTA®.

Tell your doctor about all the medicines you take, including prescription and nonprescription medicines, vitamins, and herbal supplements. Using NUCYNTA® with other medicines can cause serious side effects. The doses of some other medicines may need to be changed. Your doctor can tell you what medicines can be safely taken with NUCYNTA®. Especially tell your doctor if you take:

- Monoamine Oxidase Inhibitors (MAOIs). See "Who should not take NUCYNTA®."
- any medicine that makes you sleepy. NUCYNTA® can make you sleepy and affect your breathing. Taking these medicines together can be dangerous.

How should I take NUCYNTA®?

- Do not take NUCYNTA® unless it has been prescribed for you by your doctor.
- Take NUCYNTA® exactly as prescribed by your doctor.
- Do not change the dose of NUCYNTA® unless your doctor tells you to. Your doctor may change your dose after seeing how the medicine affects you. Do not use NUCYNTA® more often than prescribed. Call your doctor if your pain is not well controlled while taking NUCYNTA®.
- Follow your doctor's instructions about how to slowly stop taking NUCYNTA® to help lessen withdrawal symptoms.
- NUCYNTA® can be taken with or without food.

What should I avoid while taking NUCYNTA®?

- Do not drive, operate machinery, or participate in any other possibly dangerous activities until you know how you react to this medicine. NUCYNTA® can make you sleepy.
- You should not drink alcohol while using NUCYNTA®. Alcohol increases your chance of having dangerous side effects.

What are the possible side effects of NUCYNTA®?

NUCYNTA® can cause serious side effects including:

- Life-threatening breathing problems. Call your doctor right away or get emergency medical help if you:
  - have trouble breathing, or have slow or shallow breathing
  - have a slow heartbeat
  - have severe sleepiness
  - have cold, clammy skin
  - feel faint, dizzy, confused, or can not think, walk or talk normally
  - have a seizure
  - have hallucinations
- Physical Dependence. NUCYNTA® can cause physical dependence. Talk to your doctor about slowly stopping NUCYNTA® to avoid getting sick with withdrawal symptoms. You could become sick with uncomfortable symptoms because your body has become used to the medicine. Tell your doctor if you have any of these symptoms of withdrawal: feeling anxious, sweating, sleep problems, shivering, pain, nausea, tremors, diarrhea, upper respiratory symptoms, hallucinations, hair "standing on end." Physical dependence is not the same as drug addiction. Your doctor can tell you more about the differences between physical dependence and drug addiction.
- Serotonin syndrome. Serotonin syndrome is a rare, life-threatening problem that could happen if you take NUCYNTA® with Selective Serotonin Reuptake Inhibitors (SSRIs), Serotonin and Norepinephrine Reuptake Inhibitors (SNRIs), Monoamine Oxidase Inhibitors (MAOIs), triptans or certain other medicines. Call your doctor or get medical help right away if you have any one or more of the these symptoms: you feel agitated, have hallucinations, coma, rapid heart beat, feel overheated, loss of coordination, over active reflexes, nausea, vomiting, or diarrhea.
- Seizures. NUCYNTA® can cause seizures in people who are at risk for seizures or who have epilepsy. Tell your doctor right away if you have a seizure and stop taking NUCYNTA®.
- Low blood pressure. This can make you feel dizzy if you get up too fast from sitting or lying down.

The common side effects with NUCYNTA® are nausea, dizziness, vomiting, sleepiness, and itching.

Constipation is a common side effect of all opioid medicines. Talk to your doctor about the use of laxatives and stool softeners to prevent or treat constipation while taking NUCYNTA®.

Tell your doctor about any side effect that bothers you or that does not go away. These are not all the possible side effects of NUCYNTA®. For a complete list, ask your doctor or pharmacist.

Call your doctor for medical advice about side effects. You may report side effects to FDA at 1-800-FDA-1088.

How should I store NUCYNTA®?

- Store NUCYNTA® at 59ºF to 86ºF (15ºC to 30ºC). Keep NUCYNTA® tablets dry.
- Dispose of NUCYNTA® tablets you no longer need.

Keep NUCYNTA® in a safe place out of the reach of children.

General information about NUCYNTA®

Medicines are sometimes prescribed for purposes other than those listed in a Medication Guide. Do not use NUCYNTA® for a condition for which it was not prescribed. Do not give NUCYNTA® to other people, even if they have the same symptoms you have. Sharing NUCYNTA® could be harmful and is against the law.

This Medication Guide summarizes the most important information about NUCYNTA®. If you would like more information, talk with your doctor. You can ask your doctor or pharmacist for information about NUCYNTA® that is written for doctors. For more information about NUCYNTA® call 1-800-526-7736.

What are the ingredients in NUCYNTA®?

Active Ingredient: tapentadol

Inactive ingredients: microcrystalline cellulose, lactose monohydrate, croscarmellose sodium, povidone, magnesium stearate, and Opadry® II, a proprietary film-coating mixture containing polyvinyl alcohol, titanium dioxide, polyethylene glycol, talc, and aluminum lake coloring.

This Medication Guide has been approved by the U.S. Food and Drug Administration.

Revised: June 2010

Manufactured by:
Janssen Ortho, LLC
Gurabo, PR 00778

Manufactured for:
PriCara®, Division of Ortho-McNeil-Janssen Pharmaceuticals, Inc.
Raritan, NJ 08869

© Ortho-McNeil-Janssen Pharmaceuticals, Inc. 2009

Repackaged by:

Rebel Distributors Corp

Thousand Oaks, CA 91320